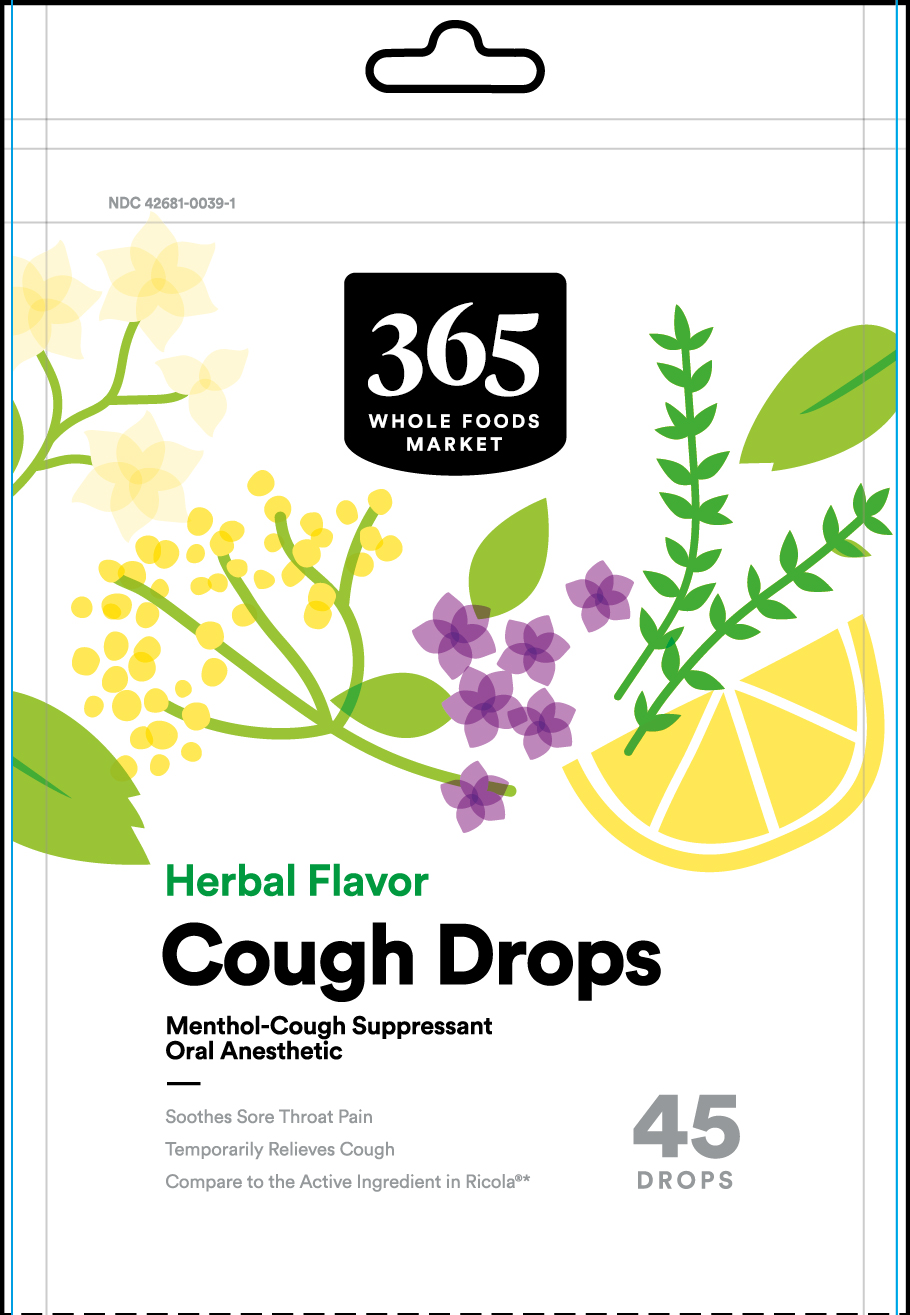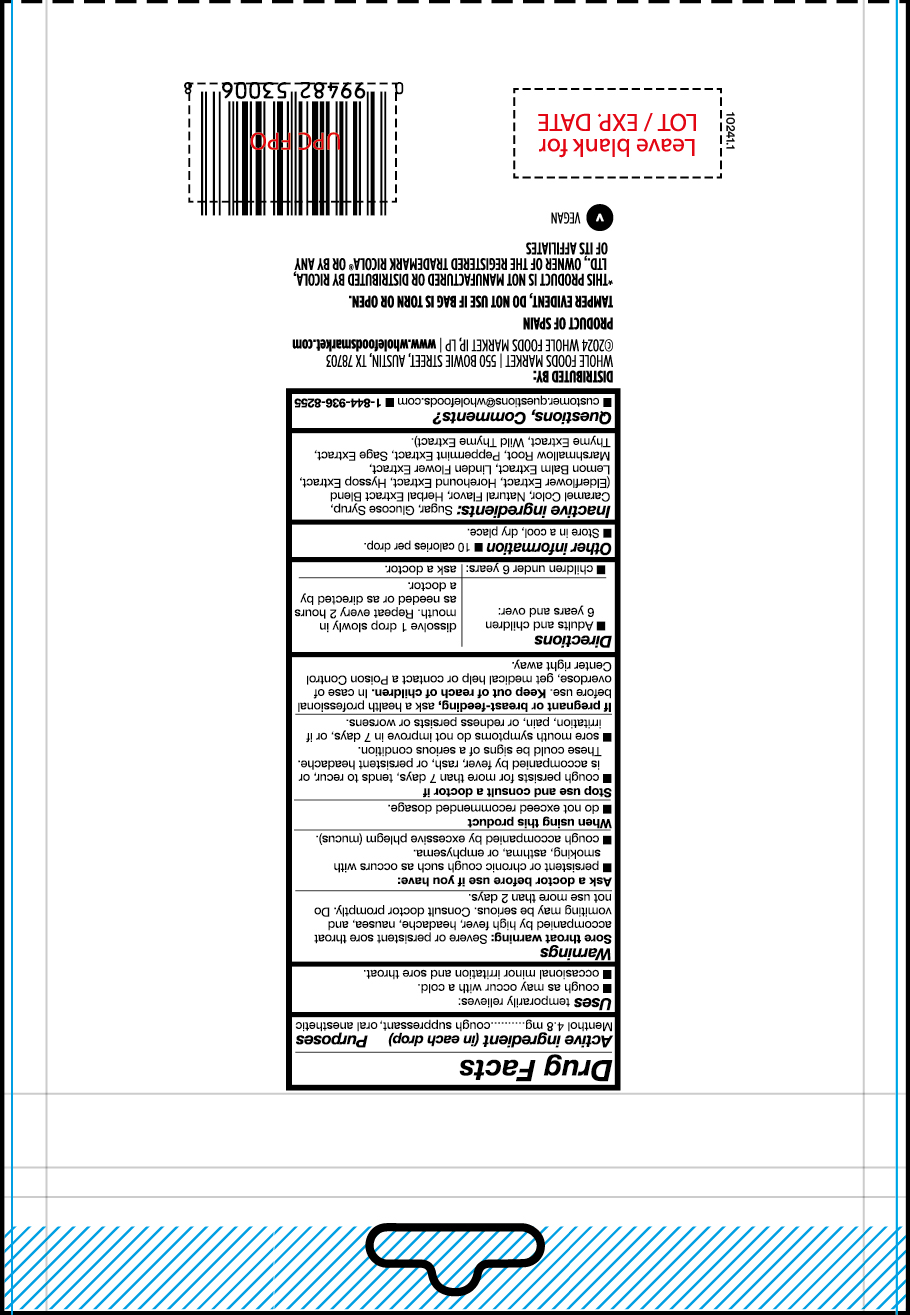 DRUG LABEL: Herbal Flavor Menthol Cough Drops
NDC: 42681-0039 | Form: PASTILLE
Manufacturer: WHOLE FOODS MARKET, INC.
Category: otc | Type: HUMAN OTC DRUG LABEL
Date: 20240802

ACTIVE INGREDIENTS: MENTHOL 4.8 mg/1 1
INACTIVE INGREDIENTS: SUGARCANE; CARAMEL; SAMBUCUS NIGRA FLOWER; CORN SYRUP; ALTHAEA OFFICINALIS FLOWER; WILD THYME; MELISSA OFFICINALIS FLOWER; HYSSOPUS OFFICINALIS FLOWERING TOP; TILIA CORDATA FLOWER; SAGE; HOREHOUND; PEPPERMINT; THYME

Herbal Flavor Menthol Cough Drops

Active ingredient 4.8 mg

Cough Suppressant

Oral anesthetic

PURPOSE

Uses temporarily relieves:

- cough as may occur with a cold
- ocassional minor irritation and sore throat

INDICATIONS AND USAGE

Uses temporarily relieves:

cough as may occur with a cold
ocassional minor irritation and sore throat

Warnings

Sore throat warning: severe or persistence sore throat accompanied by high fever, headache, nausea and vomiting may be serious. Consult a doctor promptly. Do not use more than 2 days.

Ask a doctor before use if you have

- persistent or chronic cough such as occurs with smoking, asthma or emphysema
- cough accompany by excessive phem (mucus)

Stop use and consult a doctor if

- cough persists for more than 7 days, tends to recur, or is accompanied by fever, rash or persisten headache. These could be signs of a serious condition
- sore mouth symptons do not improve in 7 days or if irritation, pain or redness persists or worsens.

PREGNANCY OR BREAST FEEDING

If pregnant or breast-feeding, ask a health professional before use.

KEEP OUT OF REACH OF CHILDREN

Keep this and all drugs out of the reach of children.

OVERDOSAGE

In case of accidental overdose, get medical help or contact a Poison Control Center right away.

Directions

- Adults and children 6 years and over: dissolve 1 drop slowly in mouth. Repeated every 2 hours as needed or as directed by a doctor.
- Children under 6 years ask a doctor

OTHER SAFETY INFORMATION

- Store in a cool and dry place.
- 10 calories per drop

INACTIVE INGREDIENT

glucose syrup, sugar, caramel color, natural flavor, herbal extract blend (elderflower extract, horehound extract, hyssop extract, lemon balm extract, linden flower extract, marshmallow root, peppermint extract, sage extractm thyme extract, wild thyme extract

QUESTIONS

Questions? or to report and adverse event call: 1-800-936-8255